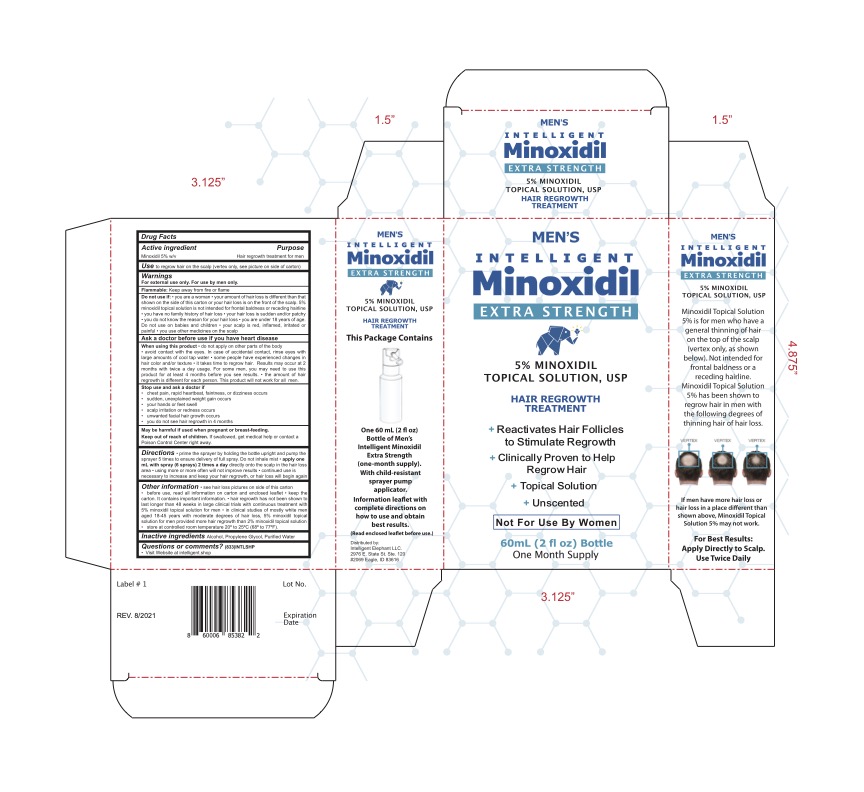 DRUG LABEL: Mens Intelligent Hair Regrowth Treatment
NDC: 81632-001 | Form: SOLUTION
Manufacturer: Intelligent Elephant LLC.
Category: otc | Type: HUMAN OTC DRUG LABEL
Date: 20230110

ACTIVE INGREDIENTS: MINOXIDIL 5 g/100 mL
INACTIVE INGREDIENTS: PROPYLENE GLYCOL; WATER; ISOPROPYL ALCOHOL

Men's Intelligent Extra Strength Minoxidil 5%

ACTIVE INGREDIENT

Minoxidil 5% w/v

PURPOSE

Hair regrowth treatment for men

USE

to regrow hair on the top of the scalp (vertex only, see picture on side of carton)

WARNINGS

For external use only. For use by men only.

Flammable: Keep away from fire or flame.

Do not use if

- You are a woman
- Your amount of hair loss is different than that shown on this carton or your hair loss is on the front of the scalp. 5% minoxidil topical solution is not intended for frontal baldness or receeding hairline
- You have no family history of hair loss
- Your hair loss is sudden and/or patchy
- Your hair loss is associated with childbirth
- You do not know the reason for your hair loss
- You are under 18 years of age. Do not use on babies or children.
- Your scalp is red, inflammed, infected, irritated, or painful
- You use other medicines on your scalp

Ask a doctor before use if you have heart disease

When using this product

- Do not apply on other parts of the body
- Avoid contact with eyes. In case of accidental contact, rinse eyes with large amounts of cool tap water.
- Some people have experienced change in hair color and/or texture. It takes time to regrow hair. Results may occur at 2 months with twice daily usage. For some men, you may need to use this product for at least 4 months before you see results.
- The amount of hair regrowth is different for each person. This product will not work for all men.

Stop use and ask doctor if

- chest pain, rapid heartbeat, faintness, or dizziness occurs
- sudden, unexplained weight gain occurs
- your hands or feet swell
- scalp irritation or redness occurs
- unwanted facial hair growth occurs
- you do not see hair regrowth in 4 months

PREGNANCY OR BREAST FEEDING

May be harmful if used when pregnant or breast-feeding.

KEEP OUT OF REACH OF CHILDREN

If swallowed, get medical help or contact a Poison Control Center right away.

DIRECTIONS

- Prime the sprayer by holding the bottle upright and pump the sprayer 5 times to ensure delivery of full spray
- Do not inhale Mist
- Apply on mL with spray (6 sprays) 2 times a day directly onto the scalp in teh airloss area
- using more or more often will not improve results
- continued use is necessary to increase and keep your hair regrowth, or hair loss will begin again

OTHER INFORMATION

• see hair loss pictures on side of this carton

• before use, read all information on carton and enclosed leaflet

• keep the carton. It contains important information.

• hair regrowth has not been shown to last longer than 48 weeks in large clinical trials with continuous treatment with 5% minoxidil topical solution for men

• in clinical studies of mostly white men aged 18-45 years with moderate degrees of hair loss, 5% minoxidil topical solution for men provided more hair regrowth than 2% minoxidil topical solution

• store at controlled room temperature 20º to 25ºC (68º to 77ºF).

INACTIVE INGREDIENT

Alcohol, Propylene Glycol, Purified Water

Questions or Comments? (833)INTLSHP

- Visit Website at intelligent.shop